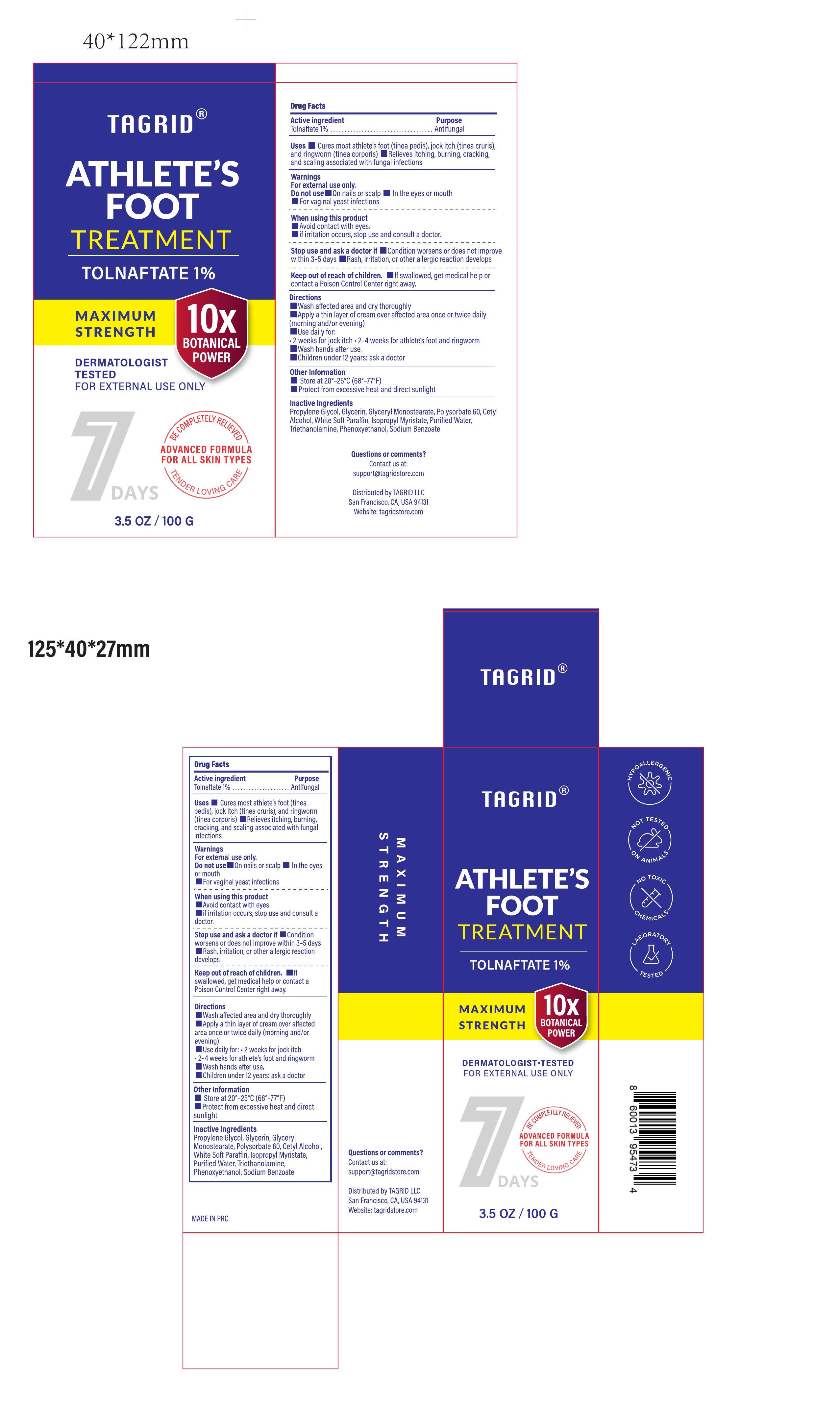 DRUG LABEL: Tagrid Athletes Foot Treament
NDC: 85384-0008 | Form: CREAM
Manufacturer: TAGRID LLC
Category: otc | Type: HUMAN OTC DRUG LABEL
Date: 20250514

ACTIVE INGREDIENTS: TOLNAFTATE 10 mg/1 g
INACTIVE INGREDIENTS: PROPYLENE GLYCOL; CETYL ALCOHOL; WHITE PETROLATUM; SODIUM BENZOATE; WATER; POLYSORBATE 60; ISOPROPYL MYRISTATE; PHENOXYETHANOL; GLYCERYL MONOSTEARATE; GLYCERIN; TRIETHANOLAMINE

Initial Drug Listing-Tagrid Athlete's Foot Treament Tolnaftate 1%

ACTIVE INGREDIENT

Tolnaftate 1%

PURPOSE

Antifungal

INDICATIONS AND USAGE

Cures most athlete's foot (tinea pedis), jock itch (tinea cruris),and ringworm (tinea corporis)

Relieves itching, buming, cracking,and scaling associated with fungal infections

WARNINGS

For external use only.

Do not use:

On nails or scalp
In the eyes or mouth
For vaginal yeast infections

WHEN USING

Avoid contact with eyes.
if irritation occurs, stop use and consult a doctor.

Stop use and ask a doctor if

Condition worsens or does not improve within 3-5 days
Rash, irritation, or other allergic reaction develops

Stop use and ask a doctor if

Condition worsens or does not improve within 3-5 days
Rash, irritation, or other allergic reaction develops

DOSAGE AND ADMINISTRATION

Direction:

Wash affected area and dry thoroughly
Apply a thin layer of cream over affected area once or twice daily (morning and/or evening)
Use daily for:
· 2 weeks for jock itch 2-4 weeks for athlete's foot and ringworm
Wash hands after use.
Children under 12 years: ask a doctor

Other Information
Store at 20°-25°C (68°-77°F)
Protect from excessive heat and direct sunlight

Questions or comments?
Contact us at:
support@tagridstore.com

Distributed by TAGRID LLC
San Francisco, CA, USA 94131
Website: tagridstore.com

INACTIVE INGREDIENT

Propylene Glycol, Glycerin, Glyceryl Monostearate, Polysorbate 60, Cetyl Alcohol, White Soft Paraffin, Isopropyl Myristate, Purified Water,Triethanolamine, Phenoxyethanol, Sodium Benzoate